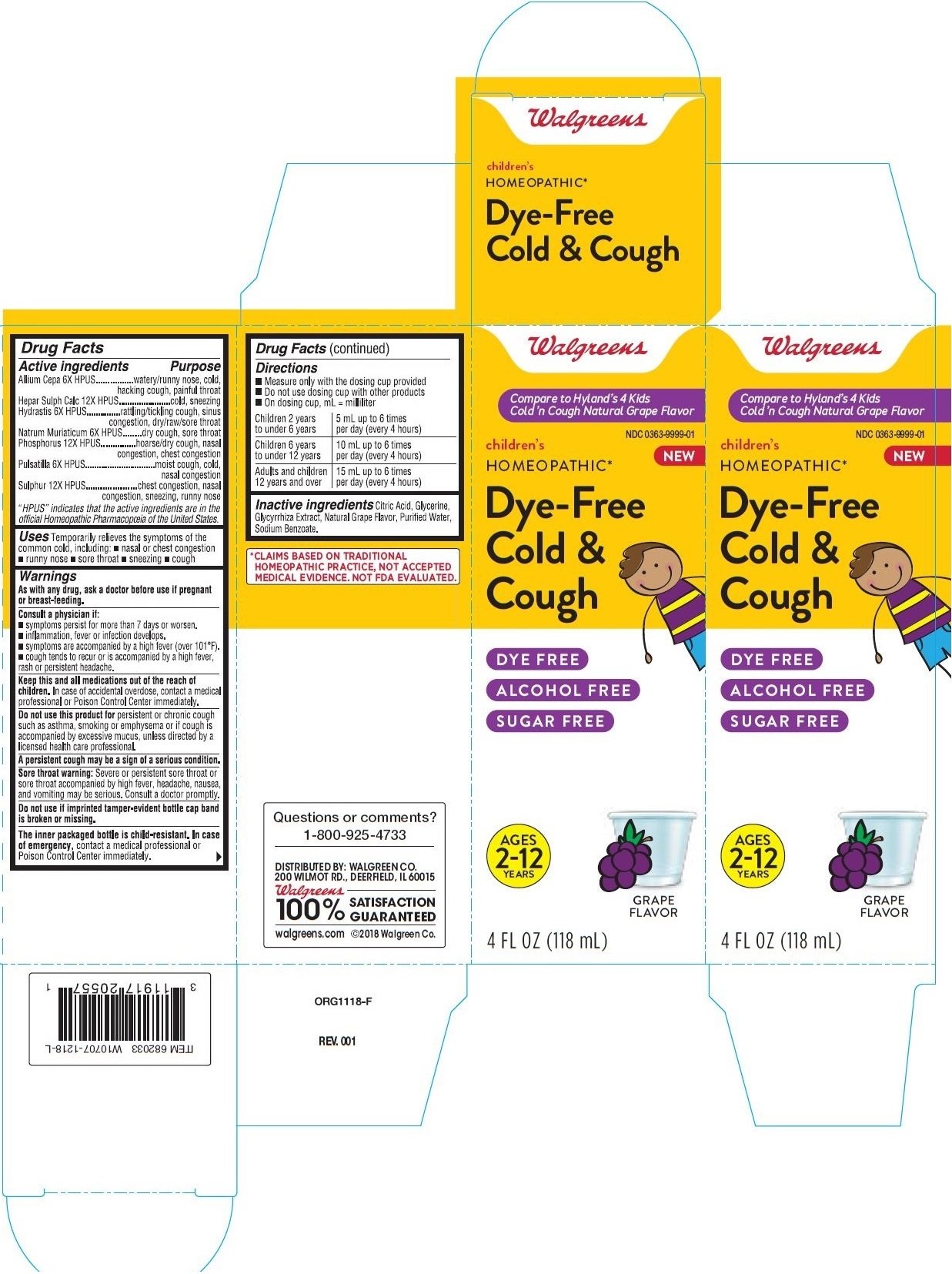 DRUG LABEL: Childrens Cold and Cough Grape Flavor
NDC: 0363-9999 | Form: LIQUID
Manufacturer: Walgreen Company
Category: homeopathic | Type: HUMAN OTC DRUG LABEL
Date: 20211221

ACTIVE INGREDIENTS: GOLDENSEAL 6 [hp_X]/1 mL; PHOSPHORUS 12 [hp_X]/1 mL; ONION 6 [hp_X]/1 mL; CALCIUM SULFIDE 12 [hp_X]/1 mL; ANEMONE PULSATILLA 6 [hp_X]/1 mL; SULFUR 12 [hp_X]/1 mL; SODIUM CHLORIDE 6 [hp_X]/1 mL
INACTIVE INGREDIENTS: CITRIC ACID MONOHYDRATE; SODIUM BENZOATE; GLYCERIN; GLYCYRRHIZA GLABRA; WATER

Walgreens Children’s Dye-Free Cold & Cough Grape Flavor

Drug Facts

Active ingredients

Allium Cepa 6X HPUS

Hepar Sulph Calc 12X HPUS

Hydrastis 6X HPUS

Natrum Muriaticum 6X HPUS

Phosphorus 12X HPUS

Pulsatilla 6X HPUS

Sulphur 12X HPUS

“HPUS” indicates that the active ingredients are in the

official Homeopathic Pharmacopœia of the United States.

PURPOSE

Allium Cepa 6X HPUS................watery/runny nose, cold,hacking cough, painful throat

Hepar Sulph Calc 12X HPUS.......................cold, sneezing

Hydrastis 6X HPUS...............rattling/tickling cough, sinus congestion, dry/raw/sore throat

Natrum Muriaticum 6X HPUS........dry cough, sore throat

Phosphorus 12X HPUS...............hoarse/dry cough, nasal congestion, chest congestion

Pulsatilla 6X HPUS...............................moist cough, cold, nasal congestion

Sulphur 12X HPUS.....................chest congestion, nasal congestion, sneezing, runny nose

Uses

Temporarily relieves the symptoms of the common cold, including: nasal or chest congestion,runny nose,sore throat,sneezing cough

Warnings

PREGNANCY OR BREAST FEEDING

As with any drug, ask a doctor before use if pregnant or breast-feeding.

Consult a physician if

- symptoms persist for more than 7 days or worsen.
- inflammation, fever or infection develops.
- symptoms are accompanied by a high fever (over 101°F).
- cough tends to recur or is accompanied by a high fever, rash or persistent headache.

Keep this and all medications out of the reach of children.

In case of accidental overdose, contact a medical professional or Poison Control Center immediately.

Do not use this product for

persistent or chronic cough such as asthma, smoking or emphysema or if cough is accompanied by excessive mucus, unless directed by a licensed health care professional.

Sore throat warning

Severe or persistent sore throat or

sore throat accompanied by high fever, headache, nausea,

and vomiting may be serious. Consult a doctor promptly.

The inner packaged bottle is child-resistant

In case of emergency, contact a medical professional or Poison Control Center immediately.

Drug Facts (continued)

Directions

- Measure only with the dosing cup provided
- Do not use dosing cup with other products
- On dosing cup, mL = milliliter

Children 2 years; to under 6 years | 5 mL up to 6 times; per day (every 4 hours)
Children 6 years; to under 12 years | 10 mL up to 6 times; per day (every 4 hours)
Adults and children; 12 years and over | 15 mL up to 6 times; per day (every 4 hours)

Inactive ingredients

Citric Acid, Glycerine, Glycyrrhiza Extract, Natural Grape Flavor, Purified Water, Sodium Benzoate.

*CLAIMS BASED ON TRADITIONAL

HOMEOPATHIC PRACTICE, NOT ACCEPTED

MEDICAL EVIDENCE. NOT FDA EVALUATED.

Questions or comments?

1-800-925-4733

DISTRIBUTED BY: WALGREEN CO.

200 WILMOT RD., DEERFIELD, IL 60015

Walgreens

100% SATISFACTION

GUARANTEED

walgreens.com ©2018 Walgreen Co.

PRINCIPAL DISPLAY PANEL-4 FL OZ (118 mL) Bottle Carton

Walgreens

Compare to Hyland’s 4 Kids

Cold ’n Cough Natural Grape Flavor

NDC 0363-9999-01

NEW

children's

HOMEOPATHIC*

Dye-Free

Cold &

Cough

DYE FREE

ALCOHOL FREE

SUGAR FREE

AGES

2-12

YEARS

GRAPE

FLAVOR

4 FL OZ (118 mL)